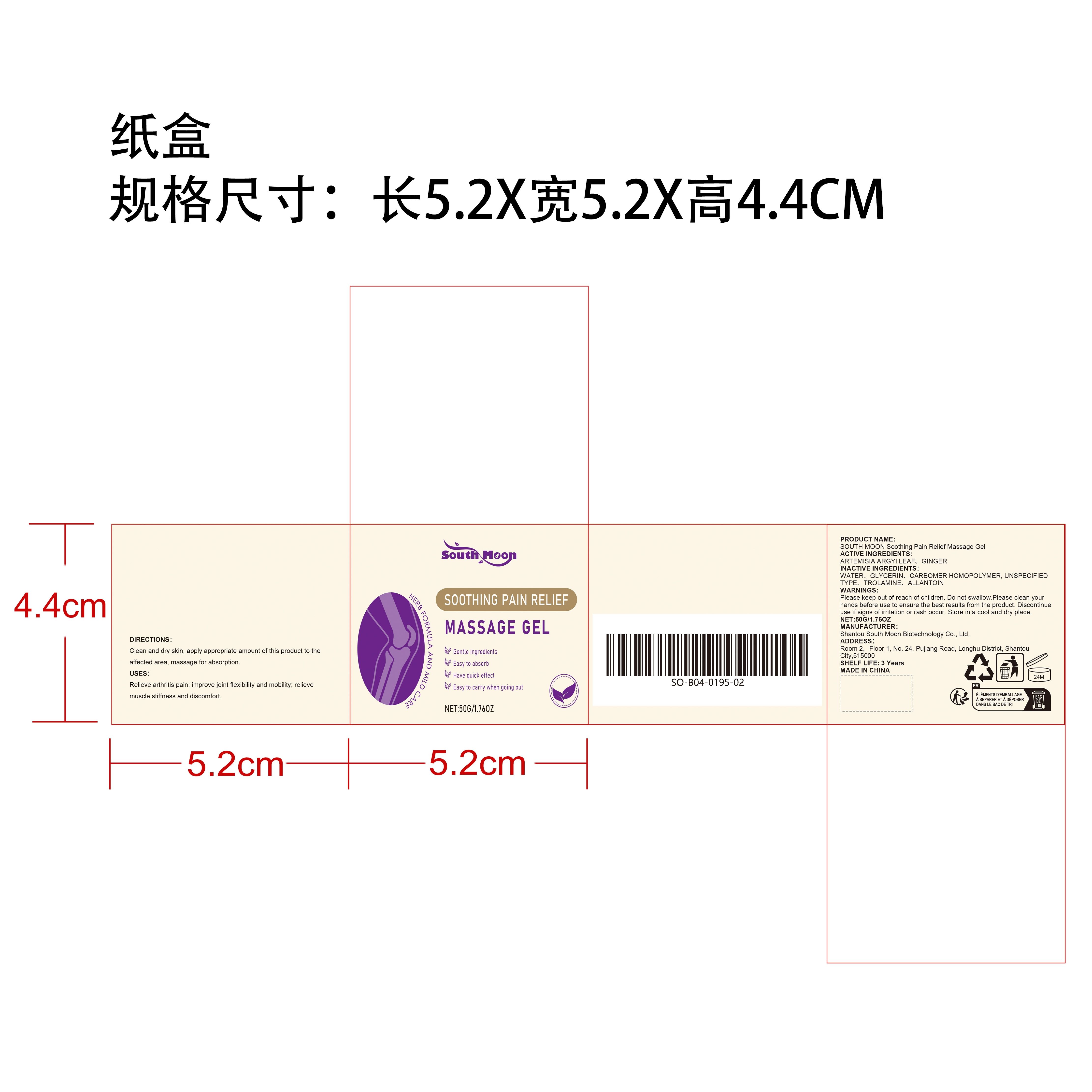 DRUG LABEL: SOUTH MOON Soothing Pain Relief Massage Gel
NDC: 84983-007 | Form: GEL
Manufacturer: Shantou South Moon Biotechnology Co., Ltd.
Category: otc | Type: HUMAN OTC DRUG LABEL
Date: 20251127

ACTIVE INGREDIENTS: ARTEMISIA ARGYI LEAF 0.01 mg/50 mg; GINGER 0.01 mg/50 mg
INACTIVE INGREDIENTS: CARBOMER HOMOPOLYMER, UNSPECIFIED TYPE 0.1 mg/50 mg; TROLAMINE 0.1 mg/50 mg; GLYCERIN 4 mg/50 mg; ALLANTOIN 0.01 mg/50 mg; WATER 45.77 mg/50 mg

ACTIVE INGREDIENT

ARTEMISIA ARGYI LEAF、GINGER

WHEN USING

Clean and dry skin, apply appropriate amount of this product to the affected area, massage for absorption.

PURPOSE

Relieve arthritis pain; improve joint flexibility and mobility; relieve muscle stiffness and discomfort.

DO NOT USE

Discontinue use if signs of irritation or rash occur.

STOP USE

Discontinue use if signs of irritation or rash occur.

KEEP OUT OF REACH OF CHILDREN

Please keep out of reach of children. Do not swallow.

WARNINGS

Please keep out of reach of children. Do not swallow.Please clean your hands before use to ensure the best results from the product. Discontinue use if signs of irritation or rash occur. Store in a cool and dry place.

STORAGE AND HANDLING

Store in a cool and dry place.

INACTIVE INGREDIENT

WATER、GLYCERIN、CARBOMER HOMOPOLYMER, UNSPECIFIED TYPE、TROLAMINE、ALLANTOIN